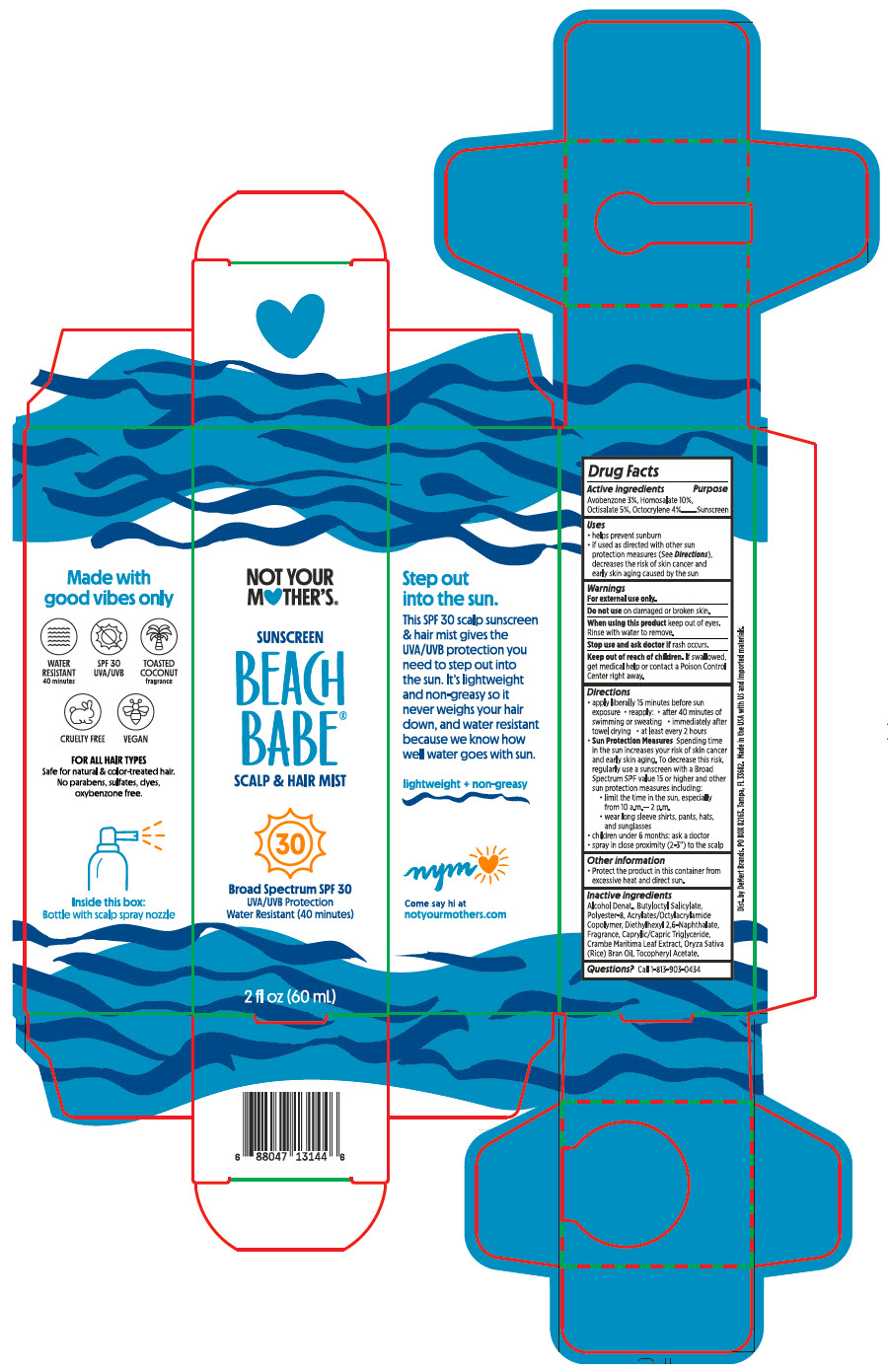 DRUG LABEL: Beach BB Scalp and Hair Protect Mist SPf30
NDC: 83187-144 | Form: SPRAY
Manufacturer: Demert Brands, LLC
Category: otc | Type: HUMAN OTC DRUG LABEL
Date: 20230228

ACTIVE INGREDIENTS: Avobenzone 3 g/100 mL; Homosalate 10 g/100 mL; Octisalate 5 g/100 mL; Octocrylene 4 g/100 mL
INACTIVE INGREDIENTS: POLYESTER-8 (1400 MW, CYANODIPHENYLPROPENOYL CAPPED); ButylOctyl Salicylate; DIETHYLHEXYL 2,6-NAPHTHALATE; Rice Bran Oil; MEDIUM-CHAIN TRIGLYCERIDES; CRAMBE MARITIMA LEAF; .ALPHA.-TOCOPHEROL ACETATE; ACRYLATE/ISOBUTYL METHACRYLATE/N-TERT-OCTYLACRYLAMIDE COPOLYMER (75000 MW); ALCOHOL; .GAMMA.-NONALACTONE; Coumarin; Benzaldehyde; PHENOXYETHANOL; ACETOPHENONE

Beach BB Scalp & Hair Protect Mist SPf30

Drug Facts

Active ingredients

Avobenzone 3% ; Homosalate 10%;Octisalate 5 %; Octocrylene 4%

Purpose

Sunscreen

Uses

Helps prevent sunburn

- If used as directed with other sun protection measures (See Directions):
- Decreases the risk of skin cancer and early skin aging caused by the sun

Warnings

For external use only.

Do Not use on damaged or broken skin

When using this product keep out of eyes. Rinse with water to remove

Stop use and ask doctor if rash occurs.

Keep out of reach of children . If swallowed, get medical help or contact a Poison Control Center right away.

Directions

- Apply liberally 15 minutes before sun exposure * reapply:
- After 40 minutes of swimming or sweating * immediately after towel drying
- At least every 2 hours
- Sun Protection Measures Spending time in the sun increases your risk of skin cancer and early skin aging. To decrease this risk, regularly use a sunscreen with a Broad Spectrum SPF value 15 or higher and other sun protection measures including:
  - Limit the time in the sun, especially from 10 am – 2 pm
  - Wear long sleeve shirts, pants, hats, and sunglasses
- Children under 6 months ask a doctor
- Spray in close proximity (2-3") to the scalp

Other information

- Protect the product in the container from excessive heat and direct sun.

Inactive Ingredients

Alcohol Denat., Butyloctyl Salicylate, Polyester-8, Acrylates/OctylAcrylamide Copolymer, Diethylhexyl 2-6-Naphthalate,Fragrance, Caprylic/Capric Triglyceride, Crambe Maritima Leaf Extract, Oryza Sativa (Rice) Bran Oil, Tocopherol Acetate.

Questions ?

Call 1-813-903-0434

Dist. by DeMert Brands. PO BOX 82163. Tampa, FL 33682.

PRINCIPAL DISPLAY PANEL - 60 mL Bottle Box

NOT YOUR
M♥THER'S®

SUNSCREEN
BEACH
BABE®
SCALP & HAIR MIST

30

Broad Spectrum SPF 30
UVA/UVB Protection
Water Resistant (40 minutes)

2 fl oz (60 mL)